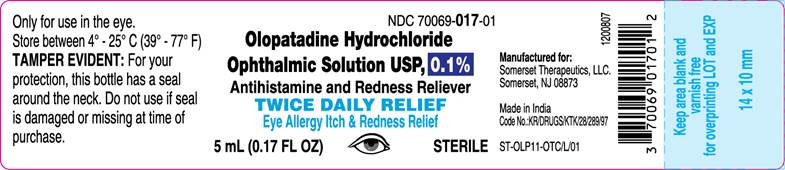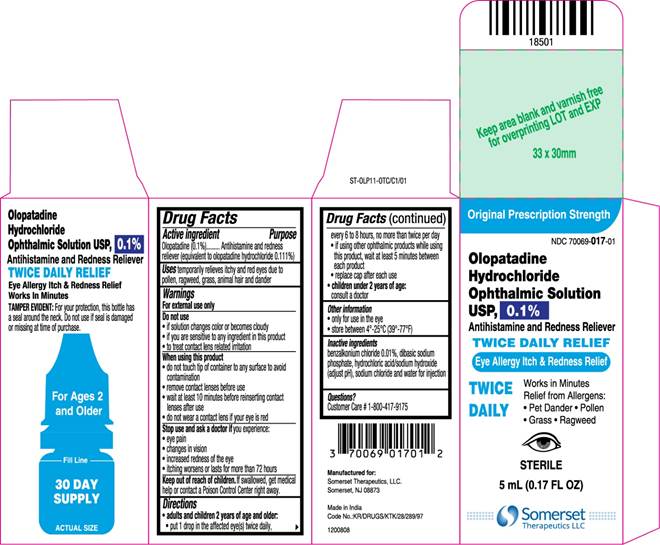 DRUG LABEL: Olopatadine
NDC: 70069-017 | Form: SOLUTION/ DROPS
Manufacturer: Somerset Therapeutics, LLC
Category: otc | Type: HUMAN OTC DRUG LABEL
Date: 20240325

ACTIVE INGREDIENTS: OLOPATADINE HYDROCHLORIDE 1 mg/1 mL
INACTIVE INGREDIENTS: SODIUM PHOSPHATE, DIBASIC; SODIUM CHLORIDE; BENZALKONIUM CHLORIDE; HYDROCHLORIC ACID; SODIUM HYDROXIDE; WATER

Olopatadine Hydrochloride Ophthalmic Solution USP, 0.1%
TWICE DAILY RELIEF

Drug Facts

Active Ingredients | Purpose
Olopatadine (0.1%) (equivalent to olopatadine hydrochloride 0.111%) | Antihistamine and Redness Reliever

INDICATIONS AND USAGE

Use temporarily relieves itchy and red eyes due to pollen, ragweed, grass, animal hair and dander

Warnings

For external use only

Do not use

- if solution changes color or becomes cloudy
- if you are sensitive to any ingredient in this product
- to treat contact lens related irritation

When using this product

- do not touch tip of container to any surface to avoid contamination
- remove contact lenses before use
- wait at least 10 minutes before reinserting contact lenses after use
- do not wear a contact lens if your eye is red

Stop use and ask a doctor if you experience:

- eye pain
- changes in vision
- increased redness of the eye
- itching worsens or lasts for more than 72 hours

Keep out of reach of children. If swallowed, get medical help or contact a Poison Control Center right away.

Directions

- adults and children 2 years of age and older:
- put 1 drop in the affected eye(s) twice daily, every 6 to 8 hours, no more than twice per day
- if using other ophthalmic products while using this product, wait at least 5 minutes between each product
- replace cap after each use
- children under 2 years of age: consult a doctor

Other information

- only for use in the eye
- store between 4°-25°C (39°-77°F)

Inactive ingredients

benzalkonium chloride 0.01%, dibasic sodium phosphate, hydrochloric acid/sodium hydroxide (adjust pH), sodium chloride and water for injection

Questions?

Customer Care # 1-800-417-9175

Manufactured for:

Somerset Therapeutics, LLC

Somerset, NJ 08873

Made in India

Code No.:KR/DRUGS/KTK/28/289/97

ST-OLP11-OTC/P/01

1200809

Container Label

NDC 70069-017-01

Olopatadine Hydrochloride Ophthalmic Solution USP, 0.1%

Antihistamine and Redness Reliever

TWICE DAILY RELIEF

Eye Allergy Itch & Redness Relief

Sterile

5 mL (0.017 FL OZ)

Carton Label

Original Prescription Strength

NDC 70069-017-01

Olopatadine Hydrochloride Ophthalmic Solution USP, 0.1%

Antihistamine and Redness Reliever

TWICE DAILY RELIEF

Eye Allergy Itch & Redness Relief

TWICE DAILY

Works in Minutes

Relief from Allergens:

• Pet Dander

• Pollen

• Grass

• Ragweed

Sterile

5 mL (0.017 FL OZ